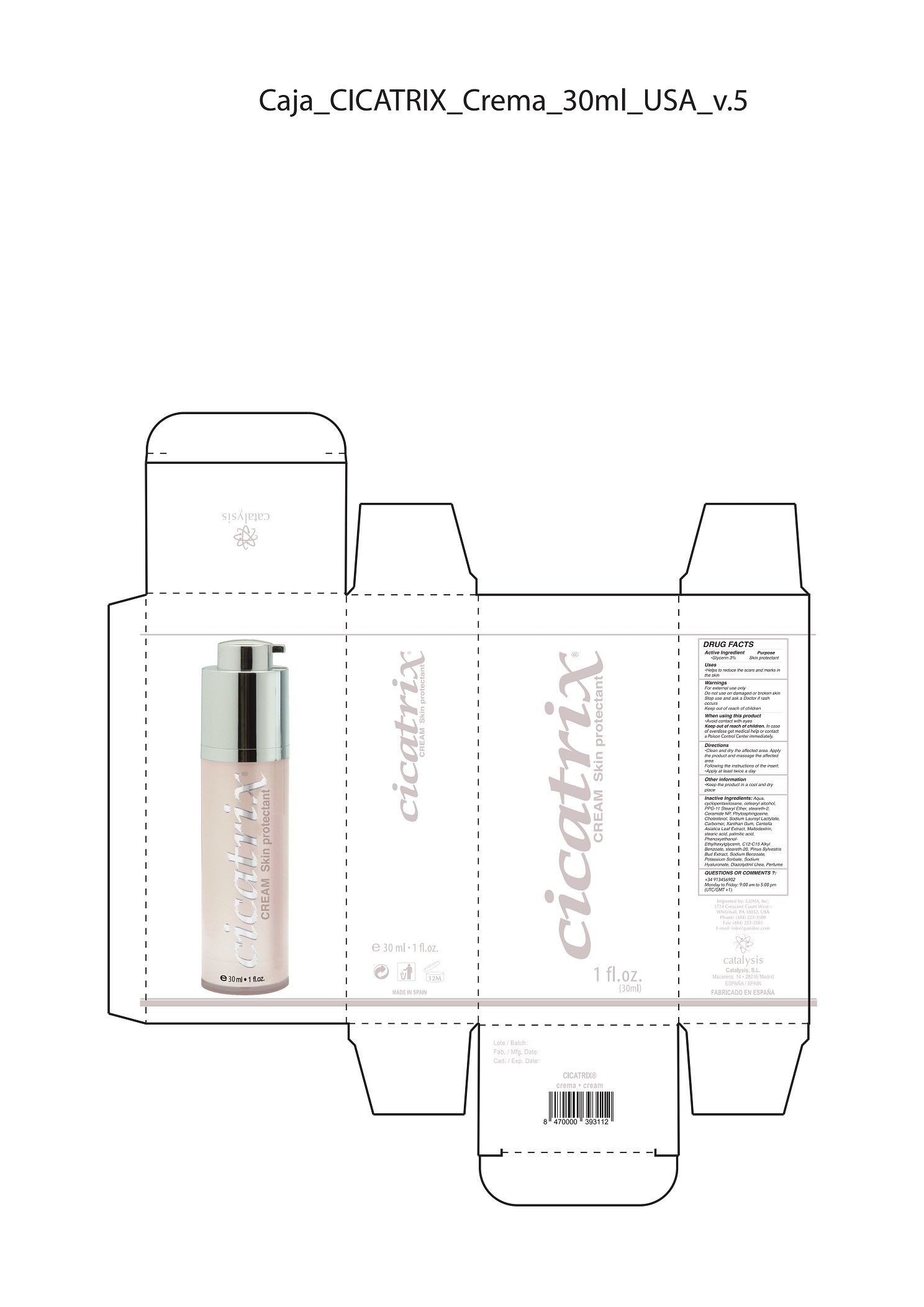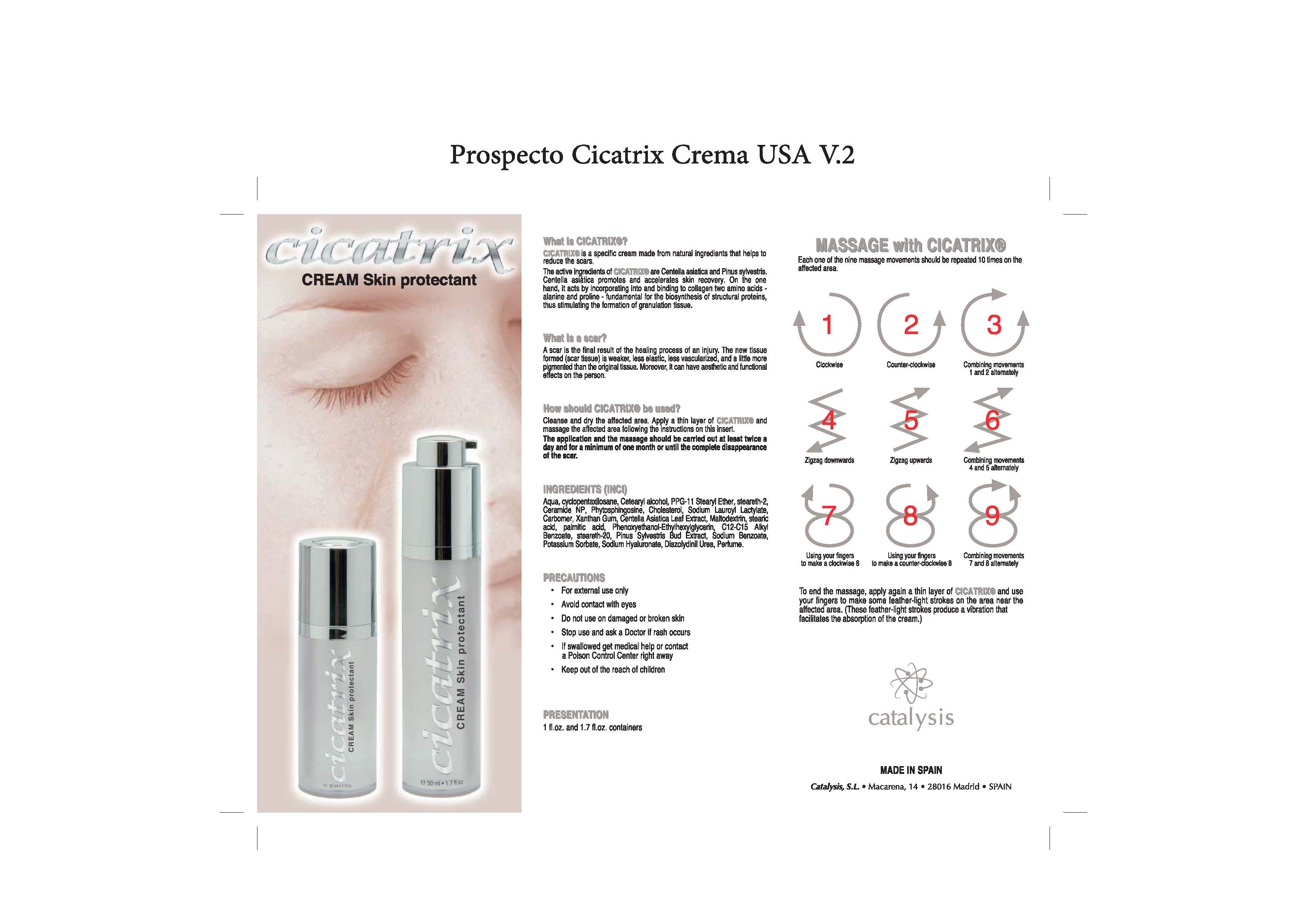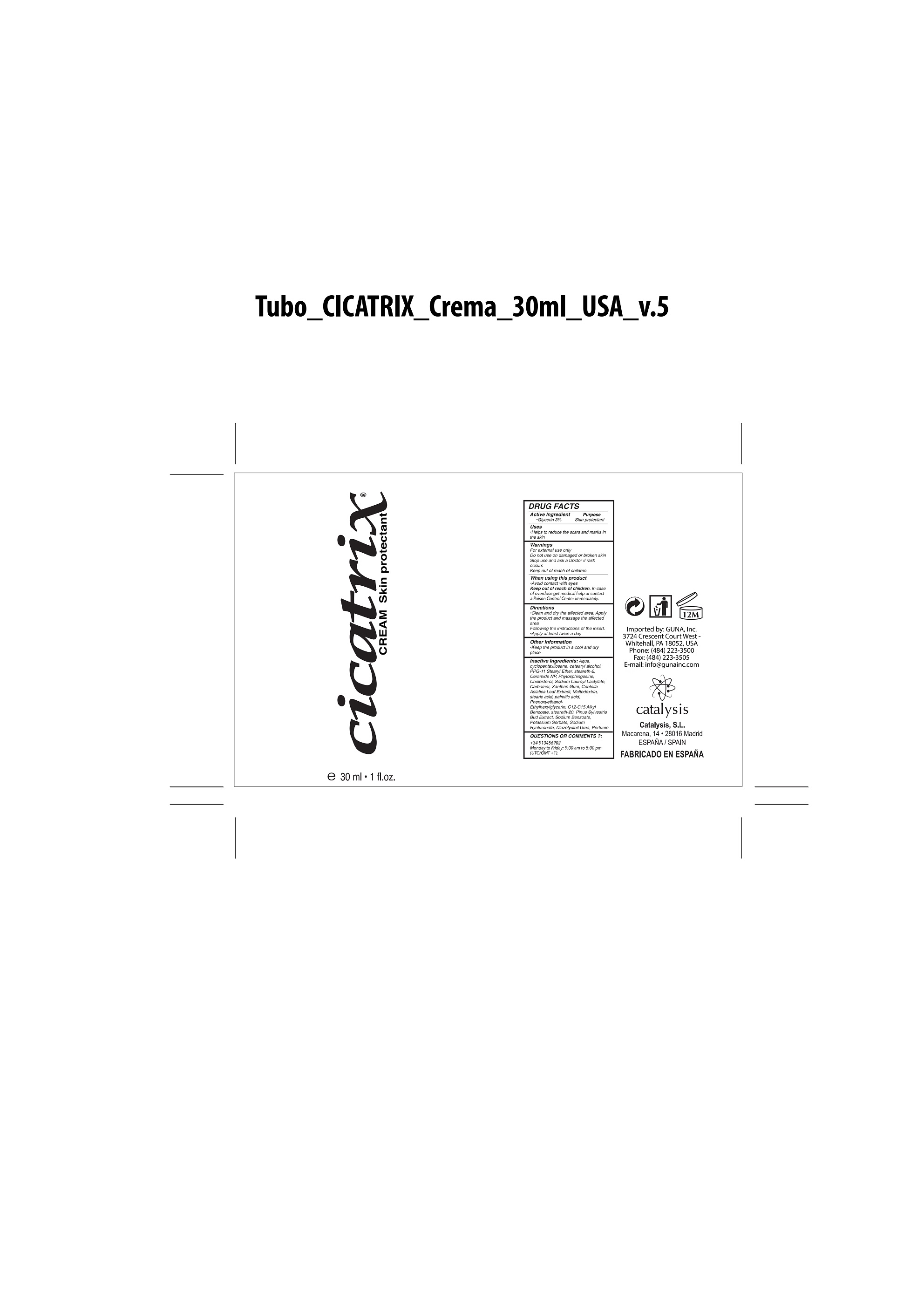 DRUG LABEL: Cicatrix Skin Protectant
NDC: 64539-015 | Form: CREAM
Manufacturer: Catalysis, SL
Category: otc | Type: HUMAN OTC DRUG LABEL
Date: 20180303

ACTIVE INGREDIENTS: GLYCERIN 3 mg/1 mL
INACTIVE INGREDIENTS: COUMARIN 0.1 mg/1 mL; HYALURONATE SODIUM 0.2 mg/1 mL; POTASSIUM SORBATE 0.12 mg/1 mL; PINE NEEDLE OIL (PINUS SYLVESTRIS) 0.12 mg/1 mL; PPG-11 STEARYL ETHER 3 mg/1 mL; STEARETH-2 2.4 mg/1 mL; CERAMIDE 3 0.25 mg/1 mL; PHYTOSPHINGOSINE 0.25 mg/1 mL; CERAMIDE 6 II 0.25 mg/1 mL; CHOLESTEROL 0.25 mg/1 mL; SODIUM LAUROYL LACTYLATE 0.25 mg/1 mL; WATER 100 mg/1 mL; CARBOXYPOLYMETHYLENE 0.45 mg/1 mL; XANTHAN GUM 0.25 mg/1 mL; CETOSTEARYL ALCOHOL 3 mg/1 mL; CENTELLA ASIATICA LEAF 0.5 mg/1 mL; STEARIC ACID 0.5 mg/1 mL; PHENOXYETHANOL 0.5 mg/1 mL; ETHYLHEXYLGLYCERIN 0.5 mg/1 mL; ALKYL (C12-15) BENZOATE 0.8 mg/1 mL; SODIUM HYDROXIDE 0.07 mg/1 mL; STEARETH-20 0.6 mg/1 mL; SODIUM BENZOATE 0.14 mg/1 mL; CYCLOMETHICONE 5 7 mg/1 mL; DIAZOLIDINYL UREA 0.2 mg/1 mL; MALTODEXTRIN 0.5 mg/1 mL; PALMITIC ACID 0.5 mg/1 mL

Cicatrix

ACTIVE INGREDIENTS PURPOSE

Glycerin 3%.................... Skin Protectant

Warnings

For external use only.

Do not use on damaged or broken skin.

When using this product keep our of the eyes. Rinse with water to remove.

Stop use and ask a doctor if rash occurs.

Keep out of reach of children

Children under 6 months: as a doctor.

WARNINGS

Stop use and ask a doctor if rash occurs

Children under 6 months: ask a doctor

Warnings

Keep out of reach of children

Questions or comments?

+ 34 M-F 9:00 am to 5:00 pm

Other Information

. keep the product in a cool and dry place

Directions

. clean and dry the affected area.

. apply the product and massage the affected area

. follow the instructions on the insert

. apply at least twice a day

DOSAGE AND ADMINISTRATION

- clean and dry the affected area.
- apply the product and massage the affected area
- follow the instructions on the insert
- apply at least twice a day

Uses

. helps to reduce the scars and marks in t he skin

Inactive Ingredients

Aqua, Cyclopentasiloxane, Cetearyl Alcohol, PPG-11 Stearyl Ether, Steareth-2, Ceramide 3, Ceramide 6II, Ceramide 1, Phytosphingosine, Cholesterol, Sodium Lauroyl Lactylate, Carbomer, Xanthan Gum, Centella Asiatica Leaf Extract, Maltodextrin, Stearic Acid, Palmitic Acid, Phenoxyethanol, Ethylhexylglycerin, C12-C15 Alkyl Benzoate, Steareth-20, Pinus Sylvestris Bud Extract, Sodium Benzoate, Potassium Sorbate, Sodium Hyaluronate, Carbomer, Diazolydinil Urea, Parfum(coumarin, hexyl cinnamal,linalool,d-limonene/dipentene/l-limonene,Geraniol,hydroxycitronellal), Sodium Hydroxide

Uses

- helps to reduce the scars and marks in t he skin